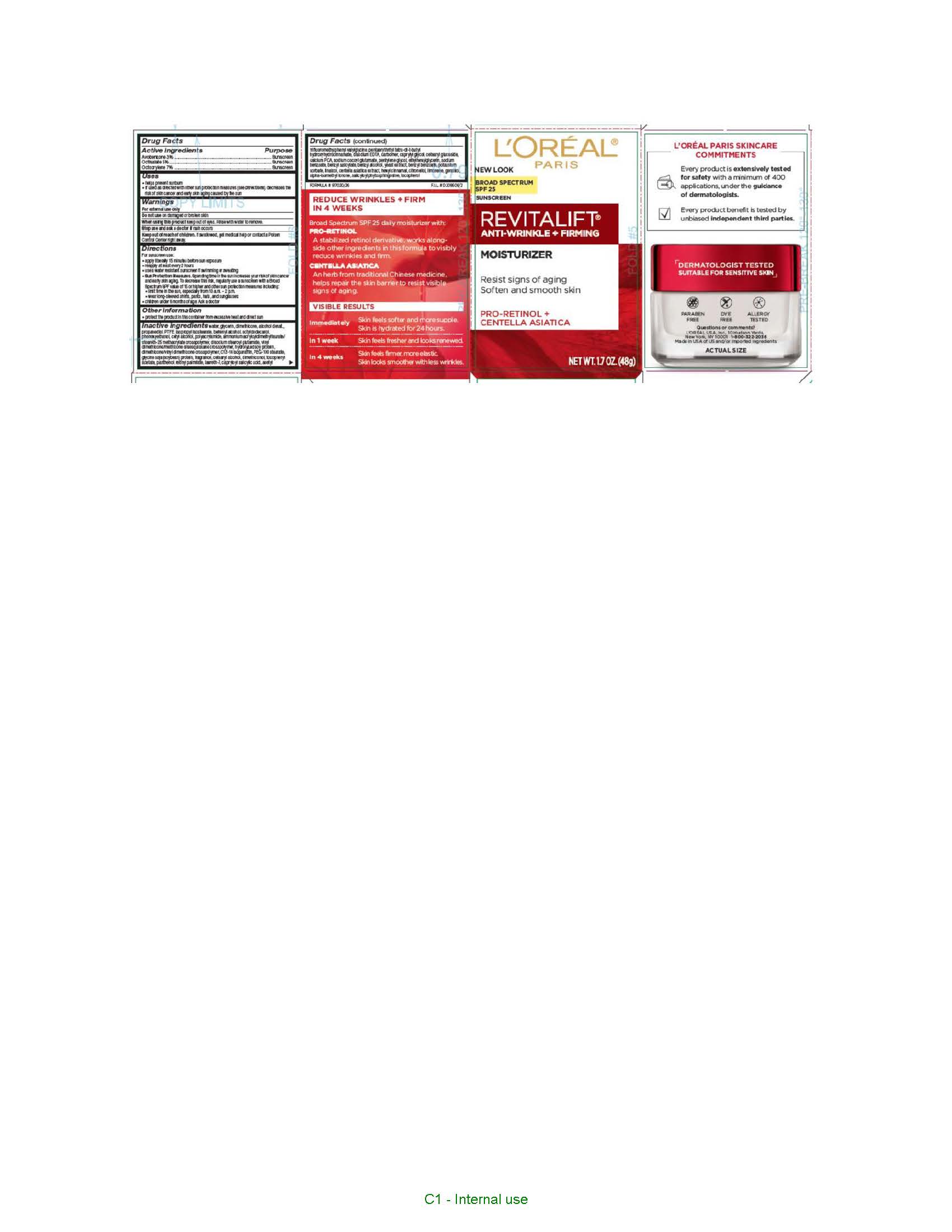 DRUG LABEL: LOREAL PARIS REVITALIFT ANTI WRINKLE FIRMING MOISTURIZER SPF 25
NDC: 49967-287 | Form: LOTION
Manufacturer: L'Oreal USA Products Inc
Category: otc | Type: HUMAN OTC DRUG LABEL
Date: 20231229

ACTIVE INGREDIENTS: AVOBENZONE 30 mg/1 mL; OCTISALATE 50 mg/1 mL; OCTOCRYLENE 70 mg/1 mL
INACTIVE INGREDIENTS: WATER; GLYCERIN; DIMETHICONE; ALCOHOL; PROPANEDIOL; POLYTETRAFLUOROETHYLENE; ISOPROPYL ISOSTEARATE; DOCOSANOL; OCTYLDODECANOL; PHENOXYETHANOL; CETYL ALCOHOL; DISODIUM STEAROYL GLUTAMATE; VINYL DIMETHICONE/METHICONE SILSESQUIOXANE CROSSPOLYMER; HYDROLYZED SOY PROTEIN (ENZYMATIC; 2000 MW); DIMETHICONE/VINYL DIMETHICONE CROSSPOLYMER (SOFT PARTICLE); C13-14 ISOPARAFFIN; PEG-100 STEARATE; SOY PROTEIN; CETOSTEARYL ALCOHOL; DIMETHICONOL (2000 CST); .ALPHA.-TOCOPHEROL ACETATE; PANTHENOL; VITAMIN A PALMITATE; LAURETH-7; CAPRYLOYL SALICYLIC ACID; PENTAERYTHRITOL TETRAKIS(3-(3,5-DI-TERT-BUTYL-4-HYDROXYPHENYL)PROPIONATE); EDETATE DISODIUM; CARBOMER HOMOPOLYMER, UNSPECIFIED TYPE; CETEARYL GLUCOSIDE; CALCIUM PIDOLATE; SODIUM COCOYL GLUTAMATE; PENTYLENE GLYCOL; ETHYLHEXYLGLYCERIN; SODIUM BENZOATE; BENZYL SALICYLATE; BENZYL ALCOHOL; YEAST, UNSPECIFIED; BENZYL BENZOATE; POTASSIUM SORBATE; LINALOOL, (+/-)-; CENTELLA ASIATICA WHOLE; .ALPHA.-HEXYLCINNAMALDEHYDE; .BETA.-CITRONELLOL, (R)-; LIMONENE, (+)-; GERANIOL; ISOMETHYL-.ALPHA.-IONONE; SALICYLOYL PHYTOSPHINGOSINE; TOCOPHEROL

Drug Facts

Active ingredients

Avobenzone 3%

Octisalate 5%

Octocrylene 7%

Purpose

Sunscreen

Uses

- helps prevent sunburn

- if used as directed with other sun protection measures (see Directions), decreases the risk of skin cancer and early skin aging caused by the sun

Warnings

For external use only

Do not use

on damaged or broken skin

When using this product

keep out of eyes. Rinse with water to remove.

Stop use and ask a doctor if

rash occurs

Keep out of reach of children.

If swallowed, get medical help or contact a Poison Control Center right away.

Directions

For sunscreen use:

● apply liberally 15 minutes before sun exposure

● reapply at least every 2 hours

● use a water resistant sunscreen if swimming or sweating

● Sun Protection Measures. Spending time in the sun increases your risk of skin cancer and early skin aging. To decrease this risk, regularly use a sunscreen with a Broad Spectrum SPF value of 15 or higher and other sun protection measures including:

● limit time in the sun, especially from 10 a.m. – 2 p.m.

● wear long-sleeved shirts, pants, hats, and sunglasses

● children under 6 months of age: Ask a doctor

Other information

protect the product in this container from excessive heat and direct sun

Inactive ingredients

water, glycerin, dimethicone, alcohol denat., propanediol, PTFE, isopropyl isostearate, behenyl alcohol, octyldodecanol, phenoxyethanol, cetyl alcohol, polyacrylamide, ammonium acryloyldimethyltaurate/steareth-25 methacrylate crosspolymer, disodium stearoyl glutamate, vinyl dimethicone/methicone silsequioxane crosspolymer, hydrolyzed soy protein, dimethicone/vinyl dimethicone crosspolymer, C13-14 isoparaffin, PEG-100 stearate, glycine soja (soybean) protein, fragrance, cetearyl alcohol, dimethiconol, tocopheryl acetate, panthenol, retinyl palmitate, laureth-7, capryloyl salicylic acid, acetyl trifluoromethylphenyl valyglycine, pentaerythrityl tetra-di-t-butyl hydroxyhydrocinnamate, disodium EDTA, carbomer, caprylyl glycol, cetearyl glucoside, calcium PCA, sodium cocoyl glutamate, pentylene glycol, ethylhexylglycerin, sodium benzoate, benzyl salicylate, benzyl alcohol, yeast extract, benzyl benzoate, potassium sorbate, linalool, centella asiatica extract, hexyl cinnamal, citronellol, limonene, geraniol, alpha-isomethyl ionone, salicyloyl phytosphingosine, tocopherol